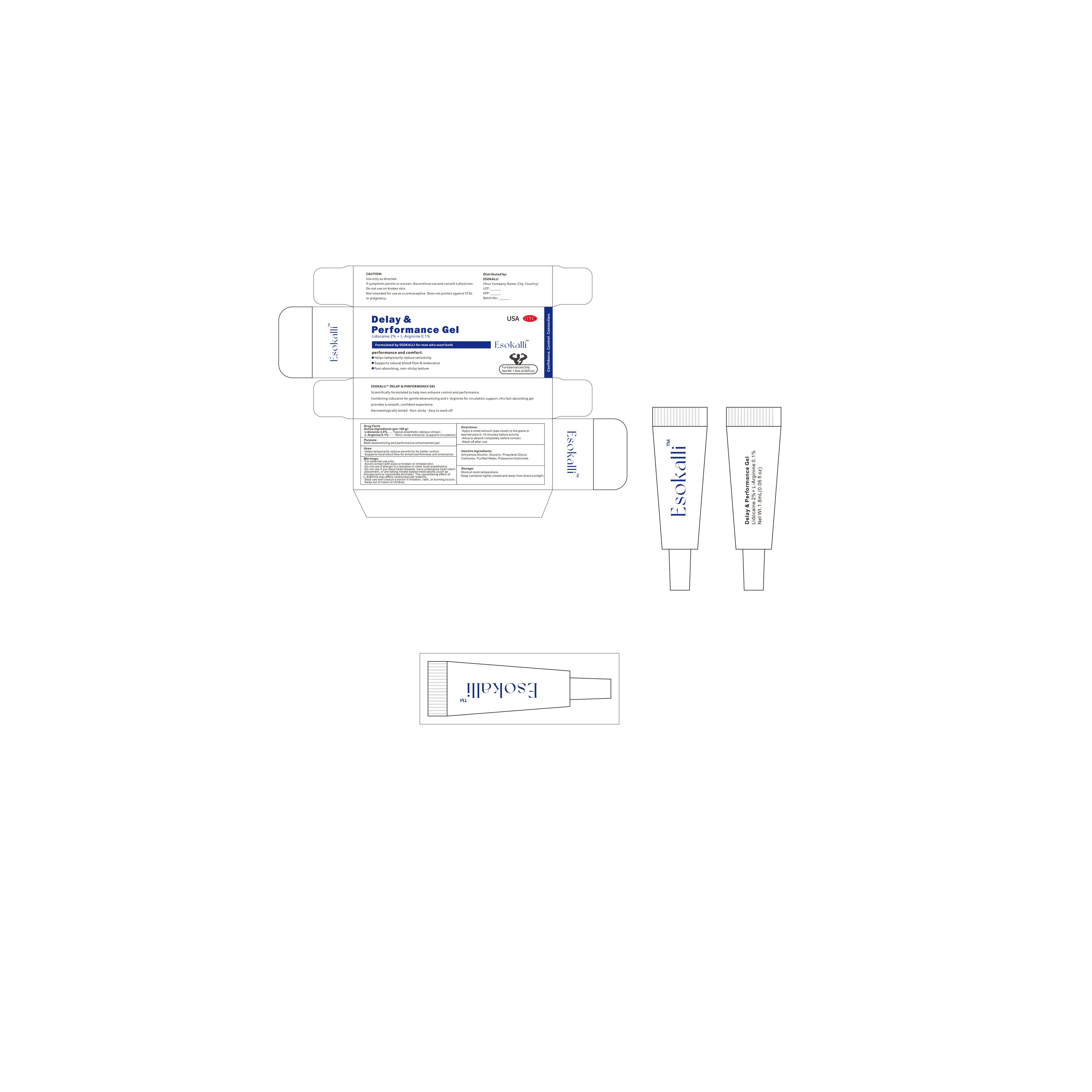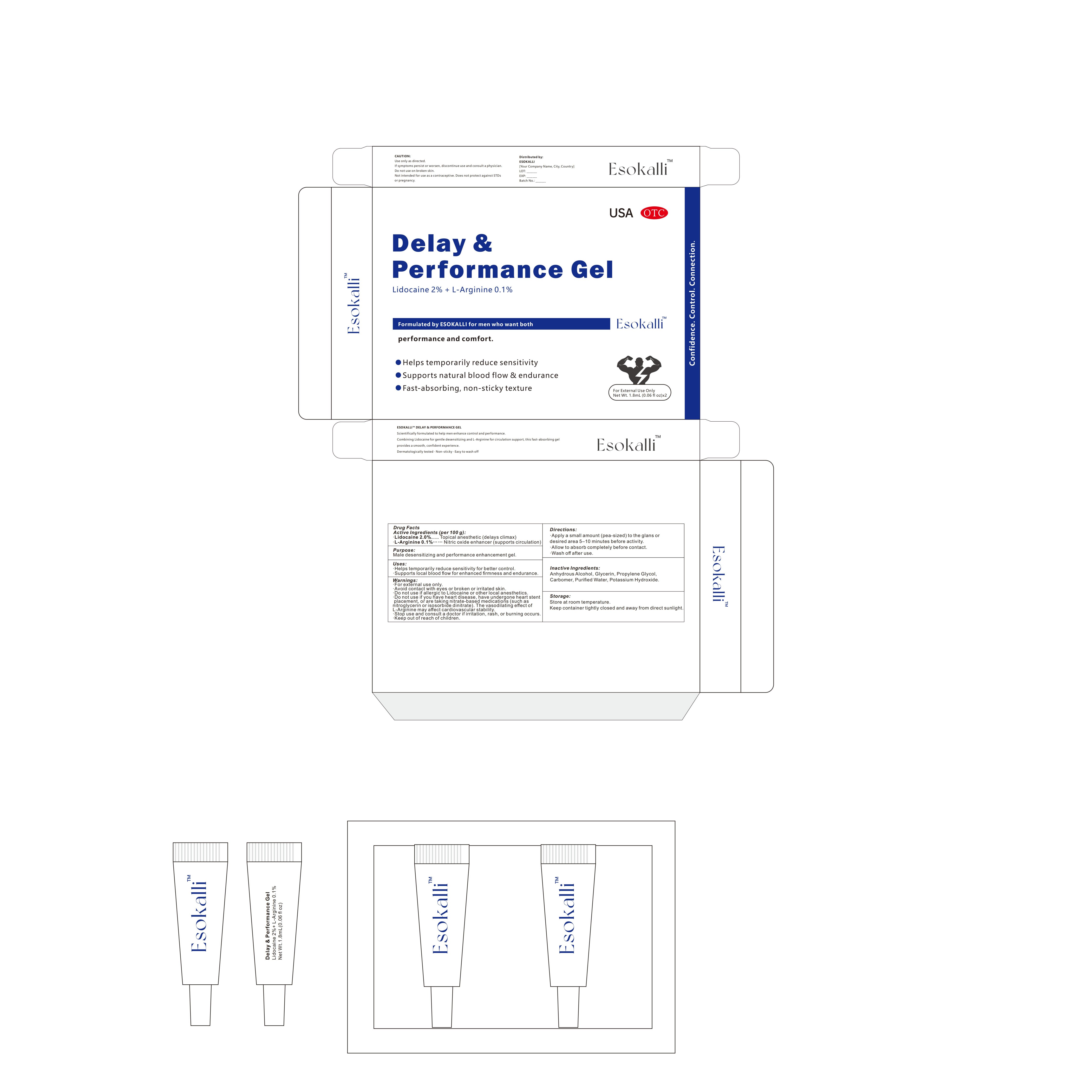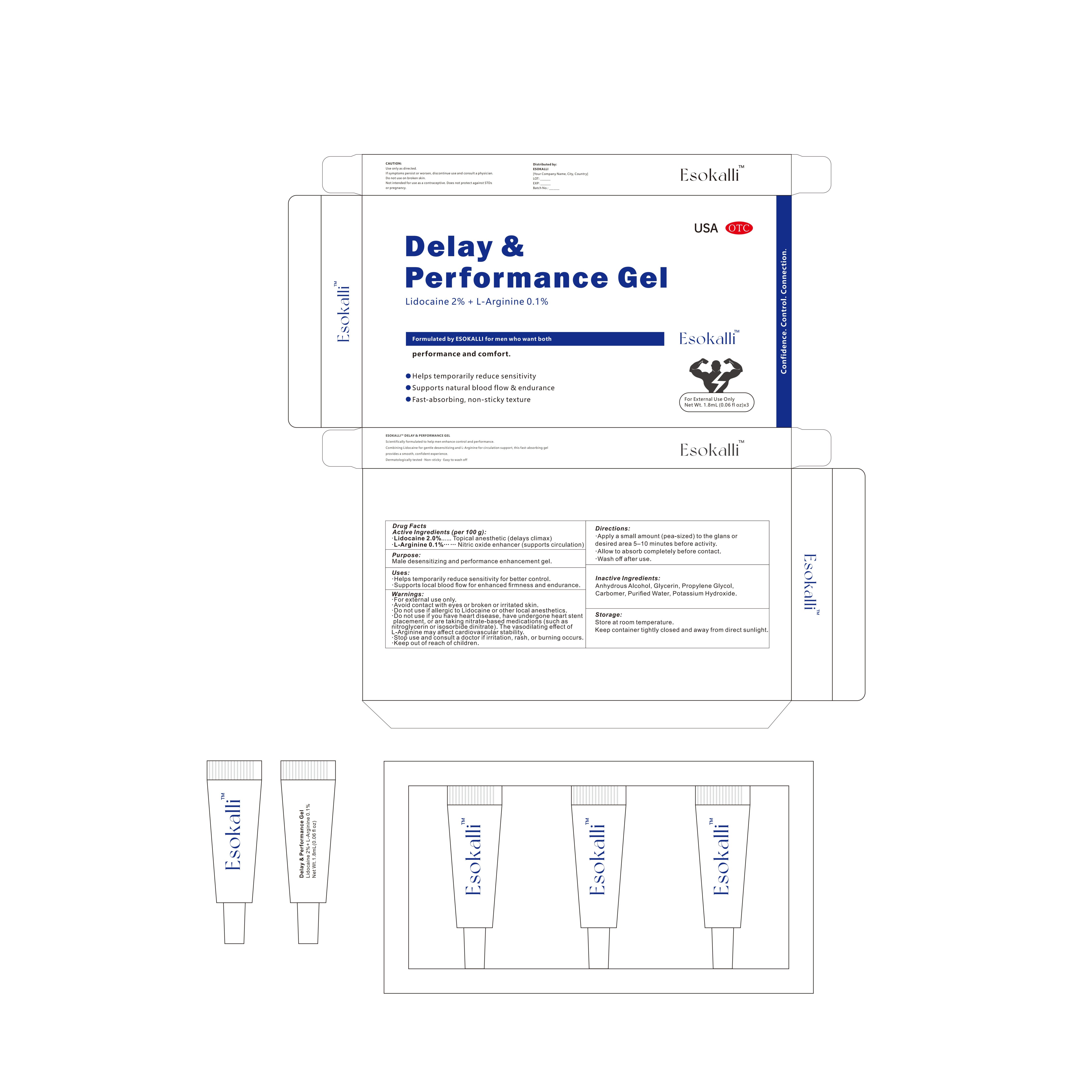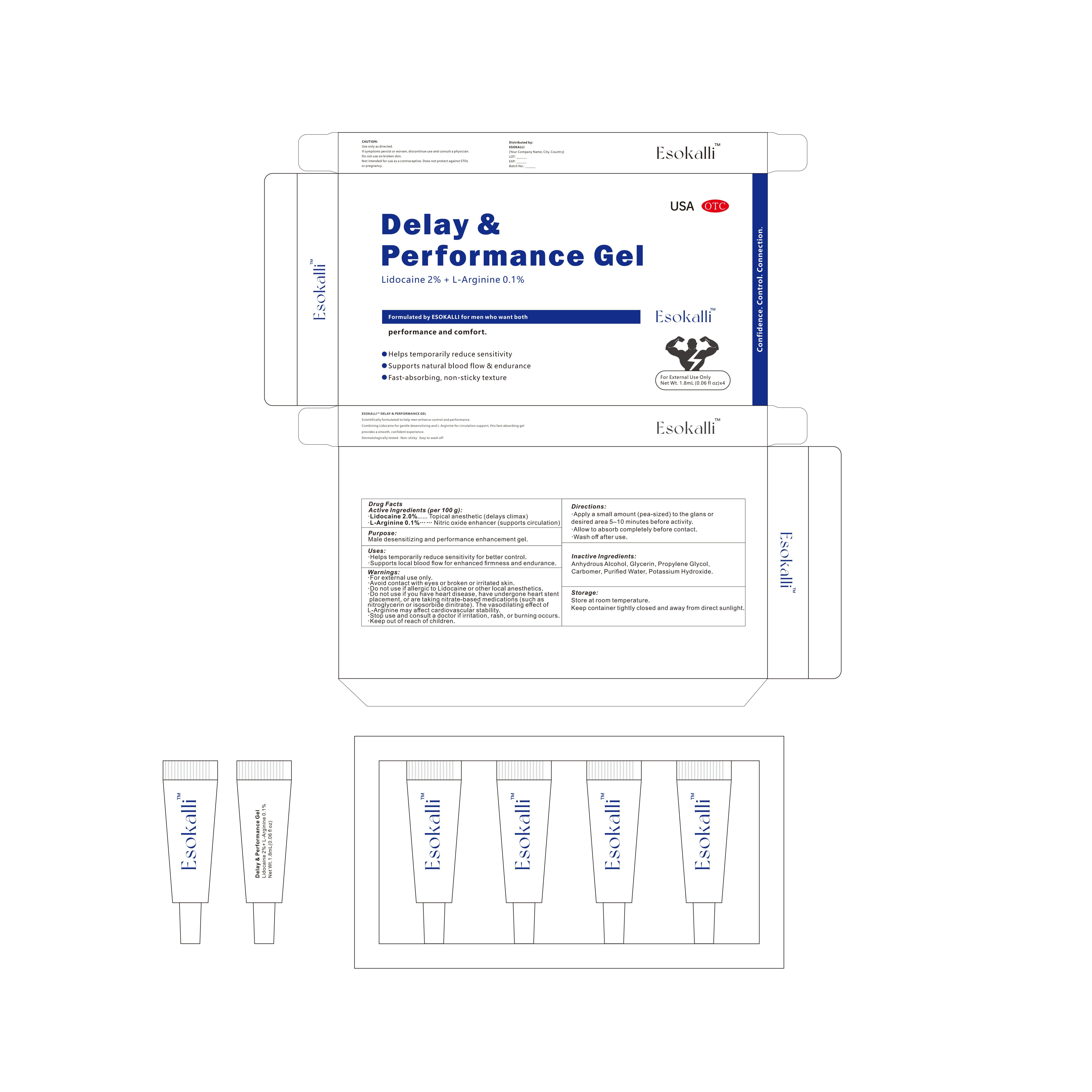 DRUG LABEL: ESOKALLI Delay Performance Gel
NDC: 84778-103 | Form: GEL
Manufacturer: Guangzhou Yixin Cross-border E-commerce Co., Ltd.
Category: otc | Type: HUMAN OTC DRUG LABEL
Date: 20251103

ACTIVE INGREDIENTS: LIDOCAINE 2 g/100 mL; ARGININE 0.1 g/100 mL
INACTIVE INGREDIENTS: PROPYLENE GLYCOL; WATER; POTASSIUM HYDROXIDE; GLYCERIN

Active Ingredients (per 100 g):

Lidocaine 2.0% — Topical anesthetic (delays climax)
L-Arginine 0.1% — Nitric oxide enhancer (supports circulation)

Purpose:

Male desensitizing and performance enhancement gel.

Uses:

Helps temporarily reduce sensitivity for better control.
Supports local blood flow for enhanced firmness and endurance.

Warnings:

For external use only.
Avoid contact with eyes or broken or irritated skin.
Do not use if allergic to Lidocaine or other local anesthetics.
Do not use if you have heart disease, have undergone heart stent placement, or are taking nitrate-based medications (such as nitroglycerin or isosorbide dinitrate). The vasodilating effect of L-Arginine may affect cardiovascular stability.
Stop use and consult a doctor if irritation, rash, or burning occurs.
Keep out of reach of children.

Do not use if you:

For external use only.
Avoid contact with eyes or broken or irritated skin.
Do not use if allergic to Lidocaine or other local anesthetics.
Do not use if you have heart disease, have undergone heart stent placement, or are taking nitrate-based medications (such as nitroglycerin or isosorbide dinitrate). The vasodilating effect of L-Arginine may affect cardiovascular stability.
Stop use and consult a doctor if irritation, rash, or burning occurs.
Keep out of reach of children.

Dosage and Administration

Apply a small amount (pea-sized) to the glans or desired area 5–10 minutes before activity.
Allow to absorb completely before contact.
Wash off after use.

When using this product you may experience:

headache, flushing, indigestion, nasal congestion, dizziness, muscle pain, back pain, nausea, rash, or visual disturbances

Stop use and ask a doctor if:

you experience chest pain, fainting, sudden vision or hearing loss
an erection lasts longer than 4 hours (priapism). This is a medical emergency.

Contraindications

Not for use in pregnant or breastfeeding women
Not for use in children under 18 years

Inactive ingredients

Anhydrous Alcohol, Glycerin, Propylene Glycol, Carbomer, Purified Water, Potassium Hydroxide.